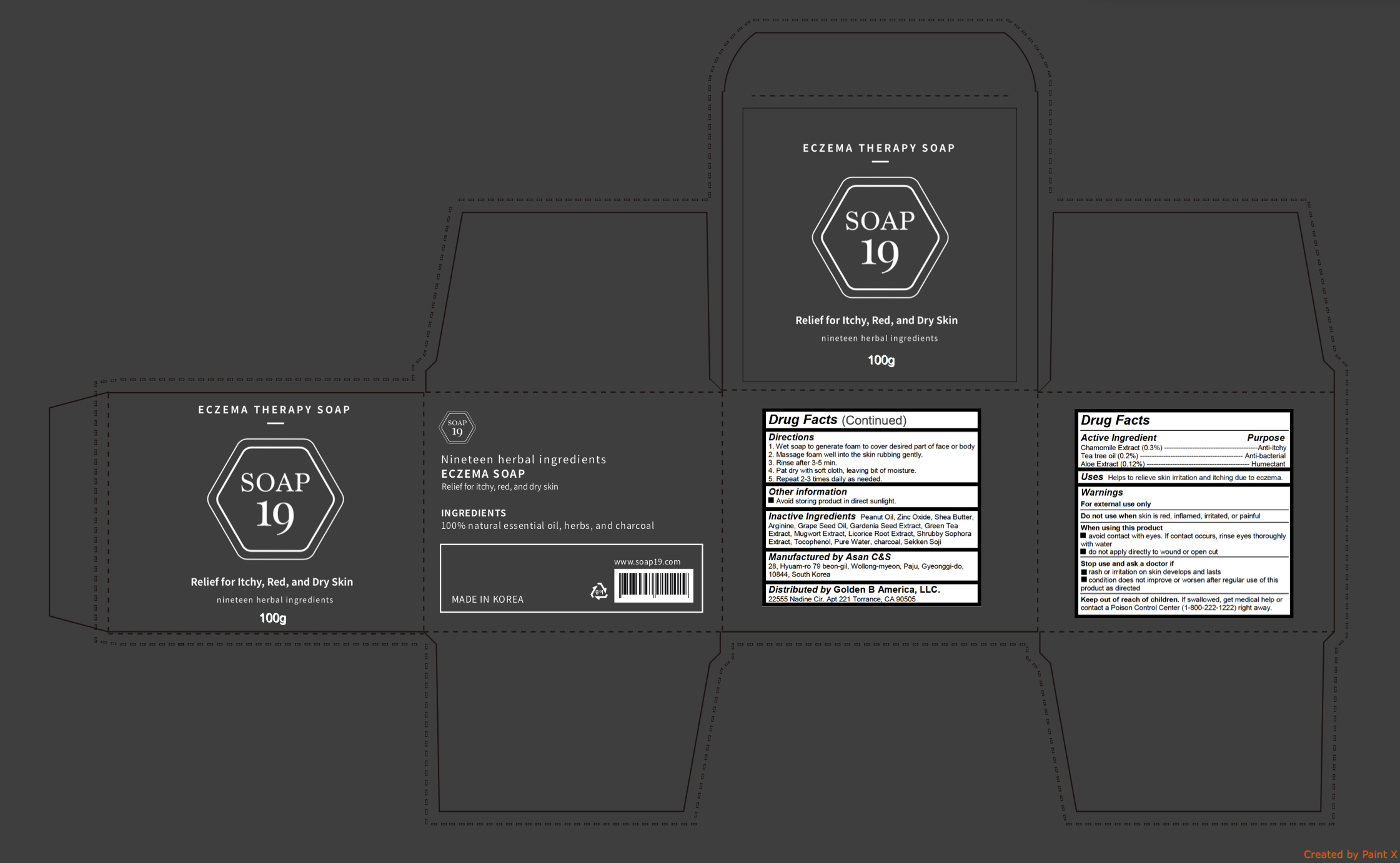 DRUG LABEL: Eczema Therapy
NDC: 72100-101 | Form: SOAP
Manufacturer: Golden B America, LLC.
Category: otc | Type: HUMAN OTC DRUG LABEL
Date: 20180313

ACTIVE INGREDIENTS: CHAMOMILE 0.3 g/100 g; TEA TREE OIL 0.2 g/100 g; ALOE 0.12 g/100 g
INACTIVE INGREDIENTS: ZINC OXIDE; SHEA BUTTER; GREEN TEA LEAF; ARTEMISIA PRINCEPS LEAF; LICORICE; TOCOPHEROL; ACTIVATED CHARCOAL; ARGININE; GRAPE SEED OIL; WATER; PEANUT OIL

Eczema Therapy Soap

Active ingredients

Chamomile Extract (0.3%)

Tea tree oil (0.2%)

Aloe Extract (0.12%)

Purpose

Anti-itchy

Anti-bacterial

Humectant

Uses

Helps to relieve skin irritation and itching due to eczema.

Warnings

For external use only

Do not use when skin is red, inflamed, irritated, or painful

When using this product

- avoid contact with eyes. If contact occurs, rinse eyes thoroughly with water
- do not apply directly to wound or open cut

Stop use and ask a doctor if

- rash or irritation on skin develops and lasts
- condition does not improve or worsen after regular use of this product as directed

Keep out reach of children

If swallowed, get medical help or contact a Poison Control Center (1-800-222-1222) right away.

Directions

1. Wet soap to generate foam to cover desired part of face or body

2. Massage foam well into the skin rubbing gently.

3. Rinse after 3-5 min.

4. Pat dry with soft cloth, leaving bit of moisture.

5. Repeat 2-3 times daily as needed.

Inactive ingredients

Peanut Oil, Zinc Oxide, Shea Butter, Arginine, Grape Seed Oil, Gardenia Seed Extract, Green Tea Extract, Mugwort Extract, Licorice Root Extract, Shrubby Sophora Extract, Tocophenol, Pure Water, charcoal, Sekken Soji